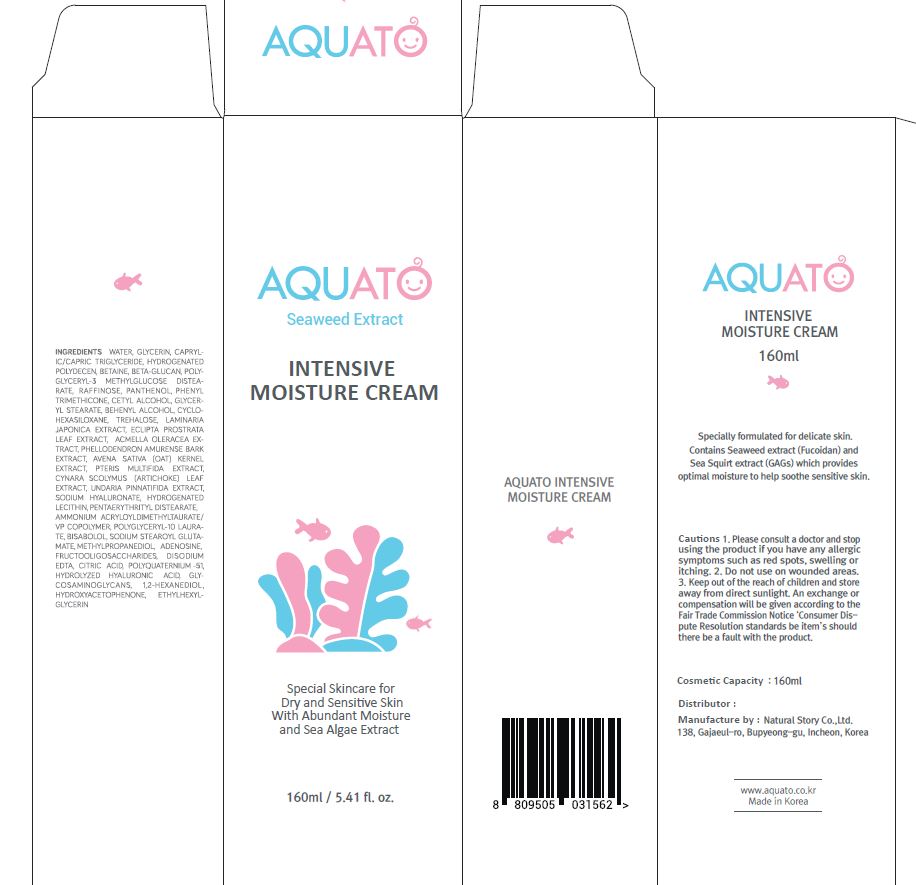 DRUG LABEL: AQUATO INTENSIVE MOISTURECREAM
NDC: 80972-0001 | Form: CREAM
Manufacturer: Natural Story Co.,Ltd.
Category: otc | Type: HUMAN OTC DRUG LABEL
Date: 20201102

ACTIVE INGREDIENTS: ADENOSINE 0.03 g/100 mL
INACTIVE INGREDIENTS: WATER

Drug Facts

ACTIVE INGREDIENT

adenosne

INACTIVE INGREDIENT

GLYCERIN
CAPRYLIC/CAPRIC TRIGLYCERIDE
HYDROGENATED POLYDECENE
BETAINE
WATER
GLYCERIN
1,2-HEXANEDIOL
BETA-GLUCAN
POLYGLYCERYL-3 METHYLGLUCOSE DISTEARATE
RAFFINOSE
PANTHENOL
WATER
DIPROPYLENE GLYCOL
GLYCERIN
LAMINARIA JAPONICA EXTRACT
ECLIPTA PROSTRATA LEAF EXTRACT
FRUCTOOLIGOSACCHARIDES
1,2-HEXANEDIOL
BETA-GLUCAN
HYDROGENATED LECITHIN
HYDROLYZED HYALURONIC ACID
PHENYL TRIMETHICONE
CETYL ALCOHOL
GLYCERYL STEARATE
CYCLOHEXASILOXANE
TREHALOSE
BEHENYL ALCOHOL
1,2-HEXANEDIOL
BISABOLOL
HYDROXYACETOPHENONE
METHYLPROPANEDIOL
GLYCERIN
WATER
POLYQUATERNIUM-51
BETA-GLUCAN
HYDROGENATED LECITHIN
PTERIS MULTIFIDA EXTRACT
CYNARA SCOLYMUS (ARTICHOKE) LEAF EXTRACT
AVENA SATIVA (OAT) KERNEL EXTRACT
1,2-HEXANEDIOL
SODIUM HYALURONATE
PROPANEDIOL
WATER
ACMELLA OLERACEA EXTRACT
ALCOHOL
WATER
PHELLODENDRON AMURENSE BARK EXTRACT
ETHYLHEXYLGLYCERIN
TOCOPHEROL
WATER
1,2-HEXANEDIOL
GLYCOSAMINOGLYCANS
WATER
1,2-HEXANEDIOL
UNDARIA PINNATIFIDA EXTRACT
DISODIUM EDTA
ADENOSINE
CITRIC ACID
PENTAERYTHRITYL DISTEARATE
SODIUM STEAROYL GLUTAMATE
AMMONIUM ACRYLOYLDIMETHYLTAURATE/VP COPOLYMER
POLYGLYCERYL-10 LAURATE

PURPOSE

special skincare for dry and sensitive skin with abundant moisture and sea algae extract

keep out of reach of the children

INDICATIONS AND USAGE

apply proper amount to the skin

Keep out of reach of children.

Store in a cool, dry place and avoid direct sunlight.

Do not inhale or drink it.

Discontinue use if skin allergy or discomfort occurs.

DOSAGE AND ADMINISTRATION

for external use only